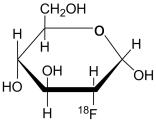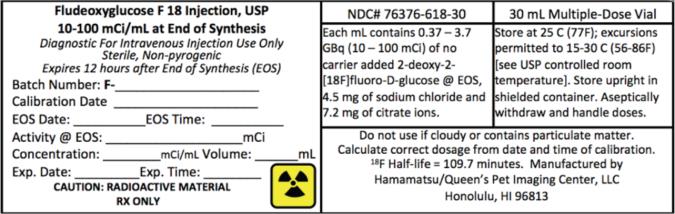 DRUG LABEL: Fludeoxyglucose F 18
NDC: 76376-618 | Form: INJECTION, SOLUTION
Manufacturer: Hamamatsu/Queen’s PET Imaging Center, LLC
Category: prescription | Type: HUMAN PRESCRIPTION DRUG LABEL
Date: 20150911

ACTIVE INGREDIENTS: FLUDEOXYGLUCOSE F-18 100 mCi/1 mL
INACTIVE INGREDIENTS: SODIUM CHLORIDE 4.5 mg/1 mL; SODIUM CITRATE 7.2 mg/1 mL

Fludeoxyglucose F 18 Injection, USP, For Intravenous Use

DESCRIPTION

Fludeoxyglucose F 18 Injection, USP is a positron emitting radiopharmaceutical containing no-carrier added radioactive 2-deoxy-2-[^18F]fluoro-D-g1ucose, which is used for diagnostic purposes in conjunction with Positron Emission Tomography (PET). It is administered by intravenous injection.

The active ingredient 2-deoxy-2-[^18F]fluoro-D-g1ucose (Fludeoxyglucose F 18), abbreviated [^18F] FDG, has a molecular formula of C6H11^18FO5 with a molecular weight of 181.26 Daltons, and has the following chemical structure:

Fludeoxyglucose F 18 Injection, USP is provided as a ready to use isotonic, sterile, pyrogen free, clear, colorless citrate buffered solution. Each mL contains between 0.37 to 3.7 GBq (10.0 – 100 mCi) of 2-deoxy-2-[^18F]fluoro-D glucose at the end of synthesis (EOS), 4.5 mg of sodium chloride and 7.2 mg of citrate ions. The pH of the solution is between 5.0 to 7.5. The solution is packaged in a multiple-dose glass vial and does not contain any preservative.

Physical Characteristics

Fluorine F 18 decays by positron (β^+) emission and has a half-life of 109.7 minutes. The principal photons useful for diagnostic imaging are the 511 keV gamma photons, resulting from the interaction of the emitted positron with an electron (Table 1).

Table 1. Principal Radiation Emission Data for Fluorine F 18
Radiation/Emission | % Per Disintegration | Mean Energy
Positron(β^+) | 96.73 | 249.8 keV
Gamma(±) [Produced by positron annihilation From: Kocher, D.C. "Radioactive Decay Tables" DOE/TIC-11026, 89 (1981).] | 193.46 | 511.0 keV

External Radiation

The specific gamma ray constant for fluorine F 18 is 6.0 R/hr/mCi (0.3 Gy/hr/kB) at 1cm. The half-value layer (HVL) for the 511 keV photons is 4.1 mm lead (Pb). A range of values for the attenuation of radiation results from the interposition of various thickness of Pb. The range of attenuation coefficients for this radionuclide is shown in Table 2. For example, the interposition of an 8.3 mm thickness of Pb, with a coefficient of attenuation of 0.25, will decrease the external radiation by 75%.

Table 2. Radiation Attenuation of 511 keV Photons by Lead (Pb) Shielding
Shield thickness (Pb) mm | Coefficient of attenuation
0 | 0.00
4.1 | 0.50
8.3 | 0.25
13.2 | 0.10
26.4 | 0.01
52.8 | 0.001

For use in correcting for physical decay of this radionuclide, the fractions remaining at selected intervals after calibration are shown in Table 3.

Table 3. Physical Decay Chart for Fluorine F 18
Minutes | Fraction Remaining
0 [Calibration time] | 1.000
15 | 0.909
30 | 0.826
60 | 0.683
110 | 0.500
220 | 0.250
440 | 0.060

CLINICAL PHARMACOLOGY

Mechanism of Action

Fludeoxyglucose F 18 is a glucose analog that concentrates in cells that rely upon glucose as an energy source, or in cells whose dependence on glucose increases under pathophysiological conditions. Fludeoxyglucose F 18 is transported through the cell membrane by facilitative glucose transporter proteins and is phosphorylated within the cell to [18F] FDG-6- phosphate by the enzyme hexokinase. Once phosphorylated it cannot exit until it is dephosphorylated by glucose-6-phosphatase. Therefore, within a given tissue or pathophysiological process, the retention and clearance of Fludeoxyglucose F 18 reflect a balance involving glucose transporter, hexokinase and glucose-6-phosphatase activities. When allowance is made for the kinetic differences between glucose and Fludeoxyglucose F 18 transport and phosphorylation (expressed as the “lumped constant” ratio), Fludeoxyglucose F 18 is used to assess glucose metabolism.

In comparison to background activity of the specific organ or tissue type, regions of decreased or absent uptake of Fludeoxyglucose F 18 reflect the decrease or absence of glucose metabolism. Regions of increased uptake of Fludeoxyglucose F 18 reflect greater than normal rates of glucose metabolism.

Pharmacodynamics

Fludeoxyglucose F 18 Injection is rapidly distributed to all organs of the body after intravenous administration. After background clearance of Fludeoxyglucose F 18 Injection, optimal PET imaging is generally achieved between 30 to 40 minutes after administration.

In cancer, the cells are generally characterized by enhanced glucose metabolism partially due to (1) an increase in the activity of glucose transporters, (2) an increased rate of phosphorylation activity, (3) a reduction of phosphatase activity or, (4) a dynamic alteration in the balance among all these processes. However, glucose metabolism of cancer as reflected by Fludeoxyglucose F 18 accumulation shows considerable variability. Depending on tumor type, stage, and location, Fludeoxyglucose F 18 accumulation may be increased, normal, or decreased. Also, inflammatory cells can have the same variability of uptake of Fludeoxyglucose F 18.

In the heart, under normal aerobic conditions, the myocardium meets the bulk of its energy requirements by oxidizing free fatty acids. Most of the exogenous glucose taken up by the myocyte is converted into glycogen. However, under ischemic conditions, the oxidation of free fatty acids stimulated, and glucose taken up by the myocyte is metabolized immediately instead of being converted into glycogen. Under these conditions, phosphorylated Fludeoxyglucose F 18 accumulates in the myocyte and can be detected with PET imaging.

Normally, the brain relies on anaerobic metabolism. In epilepsy, the glucose metabolism varies. Generally, during a seizure, glucose metabolism increases. Interictally, the seizure focus tends to be hypometabolic.

Pharmacokinetics

In four healthy male volunteers, receiving an intravenous administration of 30 seconds in duration, the arterial blood level profile for Fludeoxyglucose F 18 was described as a triexponential decay curve. The effective half-life ranges of the three phases were 0.2-0.3 minutes, 10-13 minutes with a mean and standard deviation (STD) of 11.6 ± 1.1 min, and 80-95 minutes with a mean and STD of 88 ±□ 4 min.

Plasma Protein Binding

The extent of binding of Fludeoxyglucose F 18 to plasma proteins is not known.

Metabolism

Fludeoxyglucose F 18 is transported into cells and phosphorylated to [^18F]-FDG-6-phosphate at a rate proportional to the rate of glucose utilization within that tissue. [^18F]-FDG-6-phosphate presumably is metabolized to 2-deoxy-2-[^18F]fluoro-6-phospho-D-mannose ([^18F]FDM-6-phosphate).

Fludeoxyglucose F 18 Injection may contain several impurities (e.g., 2-deoxy-2-chloro-D-glucose (ClDG)). Biodistribution and metabolism of C1DG are presumed to be similar to Fludeoxyglucose F 18 and would be expected to result in intracellular formation of 2-deoxy-2-chloro-6-phospho-D-glucose (C1DG-6-phosphate) and 2-deoxy-2-chloro-6-phospho-D-mannose (ClDM-6-phosphate). The phosphorylated deoxyglucose compounds are dephosphorylated and the resulting compounds (FDG, FDM, C1DG, and ClDM) presumably leave cells by passive diffusion.

Fludeoxyglucose F 18 and related compounds are cleared from non-cardiac tissues within 3 to 24 hours after administration. Clearance from the cardiac tissue may require more than 96 hours.

Fludeoxyglucose F 18 that is not involved in glucose metabolism in any tissue is then excreted in the urine.

Excretion

Fludeoxyglucose F 18 is cleared from most tissues within 24 hours and can be eliminated from the body unchanged in the urine. Three elimination phases have been identified in the reviewed literature. Within 33 minutes, a mean of 3.9% of the administrated radioactive dose was measured in the urine. The amount of radiation exposure of the urinary bladder at two hours post-administration suggests that 20.6% (mean) of the radioactive dose was present in the bladder.

Pharmacokinetics in Special Populations

Extensive dose range and dose adjustment studies with this drug product in normal and special populations have not been completed. In pediatric patients with epilepsy, doses given have been as low as 2.6 mCi.

The pharmacokinetics of Fludeoxyglucose F 18 Injection in renally-impaired patients have not been characterized. Fludeoxyglucose F 18 is eliminated through the renal system. Care should be taken to prevent excessive and unnecessary radiation exposure to this organ system and adjacent tissues. The effects of fasting, varying blood sugar levels, conditions of glucose intolerance, and diabetes mellitus on Fludeoxyglucose F 18 distribution in humans have not been ascertained. Diabetic patients may need stabilization of blood glucose levels on the day before and on the day of the Fludeoxyglucose F 18 Injection study.

Drug-drug interactions with Fludeoxyglucose F 18 Injection have not been evaluated.

CLINICAL TRIALS

Oncology:^1 The efficacy of Fludeoxyglucose F 18 Injection in positron emission tomography cancer imaging was demonstrated in 16 independent literature reports. These studies prospectively evaluated the sensitivity and specificity of Fludeoxyglucose F 18 for detecting malignancies. All these studies had at least 50 patients and used pathology as a standard of truth to compare the results of PET imaging with Fludeoxyglucose F 18 Injection. The studies encompassed a variety of cancers: non-small cell lung cancer, colo-rectal, pancreatic, breast, thyroid, melanoma, Hodgkin’s and non-Hodgkin’s lymphoma, and various types of metastatic cancers to lung, liver, bone, and axillary nodes. The doses in the studies ranged from 200 MBq to 740 MBq with a median and mean dose of 370 MBq.

In these studies the patients had a clinical reason for the evaluation of malignancy (e.g., the patients had an abnormality identified by a prior test and were seeking a diagnosis, or the patients had an existing diagnosis of cancer and were having further work-up or monitoring). None of these studies evaluated the use of Fludeoxyglucose F 18 Injection in routine population screening in which healthy, asymptomatic people are tested for purposes of cancer early detection. The efficacy of Fludeoxyglucose F 18 PET imaging in cancer screening, including its ability to decrease cause-specific mortality, is unknown.

In PET imaging with Fludeoxyglucose F 18 Injection, sensitivity is restricted by the biologic variability of cancer glucose utilization found in individual patients, with different cancers (see Clinical Pharmacology and Pharmacodynamic sections). In the reviewed studies, the sensitivity and specificity varied with the type of cancer, size of cancer, and other clinical parameters. Also, there were false negatives and false positives. Negative PET imaging results with Fludeoxyglucose F 18 Injection do not preclude the diagnosis of cancer and further work-up is indicated. Also, positive PET imaging results with Fludeoxyglucose F 18 Injection cannot replace biopsy to confirm a diagnosis of cancer. There are non-malignant conditions such as fungal infections, inflammatory processes, and benign tumors that had patterns of increased glucose metabolism that give rise to false-positive examinations.

Cardiology:^2 The efficacy of Fludeoxyglucose F 18 Injection for cardiac use was demonstrated in ten independent literature reports, which, in general, shared the characteristics summarized below. The studies were prospective and enrolled patients with coronary artery disease and chronic left ventricular systolic dysfunction of a mild to moderate degree. The patients were scheduled to undergo coronary revascularization with either coronary artery bypass surgery or angioplasty. Before revascularization, patients underwent PET imaging with Fludeoxyglucose F 18 Injection and perfusion imaging with other diagnostic radiopharmaceuticals. Doses of Fludeoxyglucose F 18 Injection ranged from 74-370 MBq (2-10 mCi). Segmental, left ventricular, wall-motion assessments of asynergic areas made before revascularization were compared to those made after successful revascularization to identify myocardial segments with functional recovery. Segmental wall motion assessments were made blinded to the results of metabolic/perfusion imaging, and PET image analyses were quantitative.

Left ventricular myocardial segments were predicted to have reversible loss of systolic function if they showed Fludeoxyglucose F 18 accumulation and reduced perfusion (i.e., flow-metabolism mismatch). Conversely, myocardial segments were predicted to have irreversible loss of systolic function if they showed concordant reductions in both Fludeoxyglucose F 18 accumulation and perfusion (i.e., matched defects). Diagnostic performance measures such as sensitivity, specificity, positive predictive value, and negative predictive value were calculated. None of the studies prospectively determined the degree to which mismatch, or the location of mismatch, is associated with improvements in global ventricular function, clinical symptoms, exercise tolerance, or survival.

Findings of flow-metabolism mismatch in a myocardial segment suggest that successful revascularization will restore myocardial function in that segment. However, false-positive tests occur regularly, and the decision to have a patient undergo revascularization should not be based on PET findings alone. Similarly, findings of a matched defect in a myocardial segment suggest that myocardial function will not recover in that segment, even if it is successfully revascularized. However, false-negative tests occur regularly, and the decision to recommend against coronary revascularization, or to recommend a cardiac transplant, should not be based on PET findings alone. The reversibility of segmental dysfunction as predicted with Fludeoxyglucose F 18 PET imaging depends on successful coronary revascularization. Therefore, in patients with a low likelihood of successful revascularization, the diagnostic usefulness of PET imaging with Fludeoxyglucose F 18 Injection is limited.

Epilepsy:^3 In a prospective, open label trial, Fludeoxyglucose F 18 Injection was evaluated in 86 patients with epilepsy. Each patient received a dose of Fludeoxyglucose F 18 Injection in the range of 185-370 MBq (5-10 mCi). Demographic characteristics of race and gender are not available. The mean age was 16.4 years (range: 4 months - 58 years; of these, 42 patients were <12 years and 16 patients were <2 years old). Patients had a known diagnosis of complex partial epilepsy and were under evaluation as surgical candidates for treatment of their seizure disorder. Seizure foci had been previously identified on ictal EEGs and sphenoidal EEGs. In 16% (14/87) of patients, the pre-Fludeoxyglucose F 18 Injection findings were confirmed by Fludeoxyglucose F 18; 34% (30/87) of patients, images of Fludeoxyglucose F 18 Injection provided new findings. In 32% (27/87), imaging with Fludeoxyglucose F 18 Injection was not definitive. The influence of these findings on surgical outcome, medical management, or behavior is not known.

Several other studies comparing imaging with Fludeoxyglucose F 18 Injection results to subsphenoidal EEG, MRI and/or surgical findings supported the concept that the degree of hypometabolism corresponds to areas of confirmed epileptogenic foci.

The safety and effectiveness of Fludeoxyglucose F 18 Injection to distinguish idiopathic epileptogenic foci from tumors or other brain lesions that may cause seizures have not been established.

INDICATIONS AND USAGE

Fludeoxyglucose F 18 Injection, USP is indicated in positron emission tomography (PET) imaging for assessment of abnormal glucose metabolism to assist in the evaluation of malignancy in patients with known or suspected abnormalities found by other testing modalities, or in patients with an existing diagnoses of cancer.

Fludeoxyglucose F 18 Injection, USP is indicated in positron emission tomography (PET) imaging in patients with coronary artery disease and left ventricular dysfunction, when used together with myocardial perfusion imaging, for the identification of left ventricular myocardium with residual glucose metabolism and reversible loss of systolic function.

Fludeoxyglucose F 18 Injection, USP is indicated in positron emission tomography (PET) imaging in patients for the identification of regions of abnormal glucose metabolism associated with foci of epileptic seizures.

CONTRAINDICATIONS

None known

WARNINGS

None known

PRECAUTIONS

General

Use in patients with diabetes mellitus or hyperglycemia has not been well studied. It is recommended that patients be normoglycemic when undergoing PET imaging with Fludeoxyglucose F 18 Injection.

Radiopharmaceuticals should be used only by physicians who are qualified by specific training in the safe use and handling of radionuclides (See Drug Handling section).

Information for Patients

To minimize radiation-absorbed dose to the bladder, adequate hydration should be encouraged to permit frequent voiding during the first few hours after intravenous administration of Fludeoxyglucose F 18 Injection. This may be achieved by having patients drink at least an 8 oz. glass of water prior to drug administration. To help protect themselves and others in their environment, patients should take the following precautions for 12 hours after injection: whenever possible, a toilet should be used and should be flushed several times after each use and hands should be washed thoroughly after each voiding or fecal elimination. If blood, urine or feces soil clothing, the clothing should be washed separately.

Diabetic Patients

Transport of Fludeoxyglucose F 18 into cells may be affected by fasting or by blood glucose changes associated with diabetes mellitus. Diabetic patients may need stabilization of blood glucose levels on the day before and on the day of administration of Fludeoxyglucose F 18 Injection.

Carcinogenesis, Mutagenesis, Impairment or Fertility

Studies with Fludeoxyglucose F 18 Injection have not been performed to evaluate carcinogenic potential, mutagenic potential or effects on fertility.

Teratogenic Effects: Pregnancy Category C

Animal reproduction studies have not been conducted with Fludeoxyglucose F 18 Injection. It is not known whether Fludeoxyglucose F 18 Injection can cause fetal harm when administered to a pregnant woman or can affect reproduction capacity. Therefore, Fludeoxyglucose F 18 Injection should be given to a pregnant woman only if clearly indicated.

Nursing Mothers

It is not known whether Fludeoxyglucose F 18 Injection is excreted in human milk. Caution should be exercised when Fludeoxyglucose F 18 Injection is administered to a lactating woman.

Pediatric Use

The safety and effectiveness of Fludeoxyglucose F 18 Injection in pediatric patients with epilepsy is established on the basis of studies in adult and pediatric patients. In pediatrics, the recommended dose is 2.6 mCi. The optimal dose adjustment on the basis of body size or weight has not been determined.

The safety and effectiveness of Fludeoxyglucose F 18 Injection for the evaluation of malignancy or for the identification of left ventricular myocardium with reversible loss of systolic function in pediatric patients below the age of 16 years have not been established.

See Clinical Trials section.

ADVERSE REACTIONS

The Fludeoxyglucose F 18 Injection safety database for epilepsy included of 374 patients. Of these, 245 were male and 105 were female. For 24 patients, gender was not specified. The mean age was 47.8 years (range under 2 to over 65 years). Eighteen patients were between the age of 0 and 2 years; 42 patients were between the ages of 2 and 21 years; 213 patients were between 21 and 65 years; 98 patients were older than 65 years; and the ages of 3 male patients were not specified. A racial distribution is not available. In this database, adverse drug reactions that required medical intervention were not reported. In a small, 42 patient subset of the 374 patients studied, 4 patients had transient hypotension, 6 had hypo- or hyperglycemia and 3 had transient increases in alkaline phosphatase.

Reviews of the oncology and cardiology literature did not reveal reported adverse reactions.

DOSAGE AND ADMINISTRATION

The recommended dose of Fludeoxyglucose F 18 Injection for an adult (70 kg) is 185-370 MBq (5-10 mCi), as an intravenous injection for studies of malignancy, cardiology, and epilepsy.

In general, Fludeoxyglucose F 18 Injection should be administered after patients have fasted for 4-6 hours. For cardiac use, Fludeoxyglucose F 18 Injection may be administered either to patients who have fasted or to patients who have received a glucose load (See Patient Preparation section).

The optimum rates of administration and upper safe dose for Fludeoxyglucose F 18 Injection have not been established. The time interval between doses of Fludeoxyglucose F 18 Injection should be long enough to allow substantial decay (physical and biological) of previous administrations.

The final dose for the patient should be calculated using proper decay factors from the time of the end of synthesis (EOS), and measured by a suitable radioactivity calibration system before administration. See decay factors in Table 3.

Patient Preparation: Blood glucose levels should be stabilized before Fludeoxyglucose F 18 Injection is administered. In non-diabetic patients this may be accomplished by fasting 4-6 hours before Fludeoxyglucose F 18 Injection. Diabetic patients may need stabilization of blood glucose on the day preceding and on the day of administration of Fludeoxyglucose F 18 Injection.

For cardiac imaging, administration of Fludeoxyglucose F 18 Injection to fasting patients limits the accumulation of Fludeoxyglucose F 18 to ischemic myocardium. This may make localization of the ischemic region difficult because the surrounding myocardium will not be well visualized. Conversely, administration of Fludeoxyglucose F 18 Injection to patients who have received a glucose load (e.g., 50-75 grams, 1-2 hours before administration of Fludeoxyglucose F 18 Injection) allows the surrounding, non-ischemic myocardium to be seen and facilitates localization of ischemic areas.

Imaging: Optimally, it is recommended that positron emission tomography (PET) imaging be initiated within 40 minutes of administration of Fludeoxyglucose F 18 Injection.

Static emission scans are acquired 30-100 minutes from time of injection.

OVERDOSAGE

Overdoses of Fludeoxyglucose F 18 Injection have not been reported. See Radiation Dosimetry section for related information.

DRUG HANDLING

Fludeoxyglucose F 18 Injection, USP, like other parenteral drugs, should be inspected visually for particulate matter and discoloration before administration, whenever solution and container permit. Fludeoxyglucose F 18 Injection preparations containing particulate matter or discoloration should not be administered. They should be disposed of in a safe manner, in compliance with applicable regulations.

Aseptic techniques and effective shielding should be employed in withdrawing doses for administration to patients. Waterproof gloves and effective shielding should be worn when handling the product.

The contents of each vial are sterile and non-pyrogenic. To maintain sterility, aseptic technique must be used during all operations involved in the manipulation and administration of Fludeoxyglucose F 18 Injection, USP.

Fludeoxyglucose F 18 Injection, USP should be used within 12 hours of the end of synthesis (EOS).

As with any other radioactive material, appropriate shielding should be used to avoid unnecessary radiation exposure to the patient, occupational workers, and other persons. Fludeoxyglucose F 18 Injection, USP, like other radioactive drugs, must be handled with care and appropriate safety measures should be used to minimize radiation exposure to clinical personnel. Care should be taken to minimize exposure to the patient consistent with proper patient management. Radiopharmaceuticals should be used by or under the control of physicians who are qualified by specific training and experience in the safe use and handling of radionuclides, and whose experience and training have been approved by the appropriate governmental agency authorized to license the use of radionuclides.

RADIATION DOSIMETRY

The estimated human absorbed radiation doses (rem/mCi) to a 1-year old (9.8 kg), 5-year old (19 kg), 10-year old (32 kg), 15-year old (57 kg), and adult (70 kg) from intravenous administration of Fludeoxyglucose F 18 Injection are shown in Table 4. These estimates were calculated based on human^4 data and using the data published by the International Commission on Radiological Protection^5 for Fludeoxyglucose F 18. The dosimetry data obtained and presented in this table show that there are slight variations in absorbed radiation dose for various organs in each of the age groups. These dissimilarities in absorbed radiation dose are understood to be due to developmental age variations (e.g., organ size, location, and overall metabolic rate for each age group). The identified critical organs (in descending order) across all age groups evaluated (i.e., newborn, 1, 5, 10, 15 year(s) and adults) are the urinary bladder, heart, pancreas, spleen, and lungs. The absolute values for absorbed radiation in each of these organs vary in each of the age groups.

Table 4. Estimated Absorbed Radiation Doses (rem/mCi) After Intravenous Administration of Fludeoxyglucose F 18 Injection
Organ | Newborn [MIRDOSE 2 software was used to calculate the radiation absorbed dose. Assumptions on the biodistribution based on data from Gallagher et al.((J. Nucl. Med. 18: 990-996), and Jones et al, (J. Nucl. Med, 23: 613-617).] (3.4 kg) | 1-year old (9.8 kg) | 5-year old (19 kg) | 10-year old (32 kg) | 15-year old (57 kg) | Adult (70 kg)
Bladder wall [The dynamic bladder model with a uniform voiding frequency of 1.5 hours was used.] | 4.3 | 1.7 | 0.93 | 0.60 | 0.40 | 0.32
Heart wall | 2.4 | 1.2 | 0.70 | 0.44 | 0.29 | 0.22
Pancreas | 2.2 | 0.68 | 0.33 | 0.25 | 0.13 | 0.096
Spleen | 2.2 | 0.84 | 0.46 | 0.29 | 0.19 | 0.14
Lungs | 0.96 | 0.38 | 0.20 | 0.13 | 0.092 | 0.064
Kidneys | 0.81 | 0.34 | 0.19 | 0.13 | 0.089 | 0.074
Ovaries | 0.80 | 0.8 | 0.19 | 0.11 | 0.058 | 0.053
Uterus | 0.79 | 0.35 | 0.19 | 0.12 | 0.076 | 0.062
LLI wall | 0.69 | 0.28 | 0.15 | 0.097 | 0.060 | 0.051
Liver | 0.69 | 0.31 | 0.17 | 0.11 | 0.076 | 0.058
Gallbladder wall | 0.69 | 0.26 | 0.14 | 0.093 | 0.059 | 0.049
Small intestine | 0.68 | 0.29 | 0.15 | 0.096 | 0.060 | 0.047
ULI wall | 0.67 | 0.27 | 0.15 | 0.090 | 0.057 | 0.046
Stomach wall | 0.65 | 0.27 | 0.14 | 0.089 | 0.057 | 0.047
Adrenals | 0.65 | 0.28 | 0.15 | 0.095 | 0.061 | 0.048
Testes | 0.64 | 0.27 | 0.14 | 0.085 | 0.052 | 0.041
Red marrow | 0.62 | 0.26 | 0.14 | 0.089 | 0.057 | 0.047
Thymus | 0.61 | 0.26 | 0.14 | 0.086 | 0.056 | 0.044
Thyroid | 0.61 | 0.26 | 0.13 | 0.080 | 0.049 | 0.039
Muscle | 0.58 | 0.25 | 0.13 | 0.078 | 0.049 | 0.039
Bone surface | 0.57 | 0.24 | 0.12 | 0.079 | 0.052 | 0.041
Breast | 0.54 | 0.22 | 0.11 | 0.068 | 0.043 | 0.034
Skin | 0.49 | 0.20 | 0.10 | 0.060 | 0.037 | 0.030
Brain | 0.29 | 0.13 | 0.09 | 0.078 | 0.072 | 0.070
Other tissues | 0.59 | 0.25 | 0.13 | 0.083 | 0.052 | 0.042

REFERENCES

1. See March 10, 2000 Federal Register, Docket No. 00N-0553, pp. 12999-13010
2. See March 10, 2000 Federal Register, Docket No. 00N-0553, pp. 12999-13010
3. See NDA #020306
4. Jones, S. C., A. Alavi, Christman, D., Montanez, I., Wolf, A.P. and Reivich, M. (1982).“The Radiation Dosimetry of 2-F-18 fluoro-2-deoxyglucose in Man”. J. Nucl. Me d. 23, 613-617.
5. ICRP Publication 53,Volume 18, No. l, 1987, page 76

HOW SUPPLIED

Fludeoxyglucose F 18 Injection, USP is supplied in a multi-dose septum capped 30 mL glass vial containing between 0.37 – 3.7 GBq/mL (10 - 100 mCi/mL), of no carrier added 2-deoxy-2 [^18F]fluoro-D-glucose, at end of synthesis, in approximately 24 mL.

NDC# 76376 - 618- 30

This radiopharmaceutical is licensed by the Nuclear Regulatory Commission, for distribution to entities licensed pursuant to 10 CFR 35.200.

STORAGE

Store Fludeoxyglucose F 18 Injection, USP at 25°C (77°F); excursions permitted to 15-30°C (59-86°F).

Store Fludeoxyglucose F 18 Injection, USP multiple-dose vial upright in a lead shielded container.

Store and dispose of Fludeoxyglucose F 18 Injection, USP in accordance with the regulations and a general license, or its equivalent, of an Agreement State or a Licensing State.

Expiration Date and Time

The expiration date and time are provided on the container label. Fludeoxyglucose F 18 Injection, USP should be used within 12 hours from the time of the end of synthesis (EOS).

Caution: Federal Law Prohibits Dispensing Without Prescription

Manufactured and Distributed by:
Hamamatsu/Queen’s PET Imaging Center, LLC
1301 Punchbowl Street
Honolulu, HI 96813

PRINCIPAL DISPLAY PANEL

NDC# 76376-618-30
30 mL Multiple-Dose Vial
Fludeoxyglucose F 18 Injection, USP